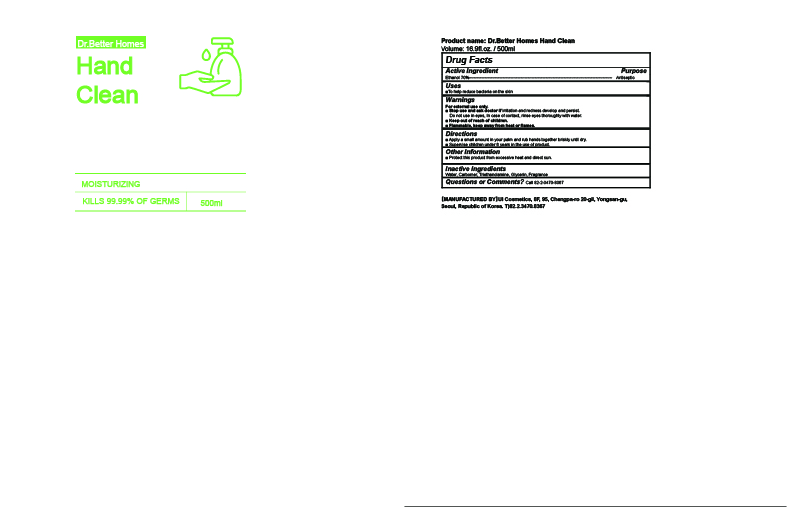 DRUG LABEL: Dr.Better Homes Hand Clean
NDC: 75615-0010 | Form: GEL
Manufacturer: UI COSMETICS CO., LTD
Category: otc | Type: HUMAN OTC DRUG LABEL
Date: 20210119

ACTIVE INGREDIENTS: ALCOHOL 70 g/100 mL
INACTIVE INGREDIENTS: TROLAMINE; GLYCERIN; WATER

75615-0010

ACTIVE INGREDIENT

Alcohol

INACTIVE INGREDIENT

Water, Glycerin, Carbomer, Triethanolamine, Fragrance

PURPOSE

Antiseptic

KEEP OUT OF REACH OF THE CHILDREN

INDICATIONS AND USAGE

For the external use only

Do not use on the following body parts.
Around the eyes and ears, in the oral cavity, a wide range of body parts and damaged skin (may have irritating effects)
If the following symptoms appear, stop using them immediately and consult a doctor or pharmacist.

Symptoms of skin irritation

Other precautions

For external use only
Be careful not to get into your eyes, and if so, rinse well with clean water and consult a doctor or pharmacist.
Be careful not to inhale vapor when using it extensively or for a long time. (If you drink ethanol vapor in large quantities or repeatedly, irritation to the mucous membrane, headache, etc. may occur).
When repeated use on the same site, be careful as the skin may become rough due to degreasing.
When used in sealed bandages, cast bandages, packs, etc., irritation symptoms may appear.
Do not use for any other purpose.

DOSAGE AND ADMINISTRATION

Put a suitable amount on your hand and rub it well to dry